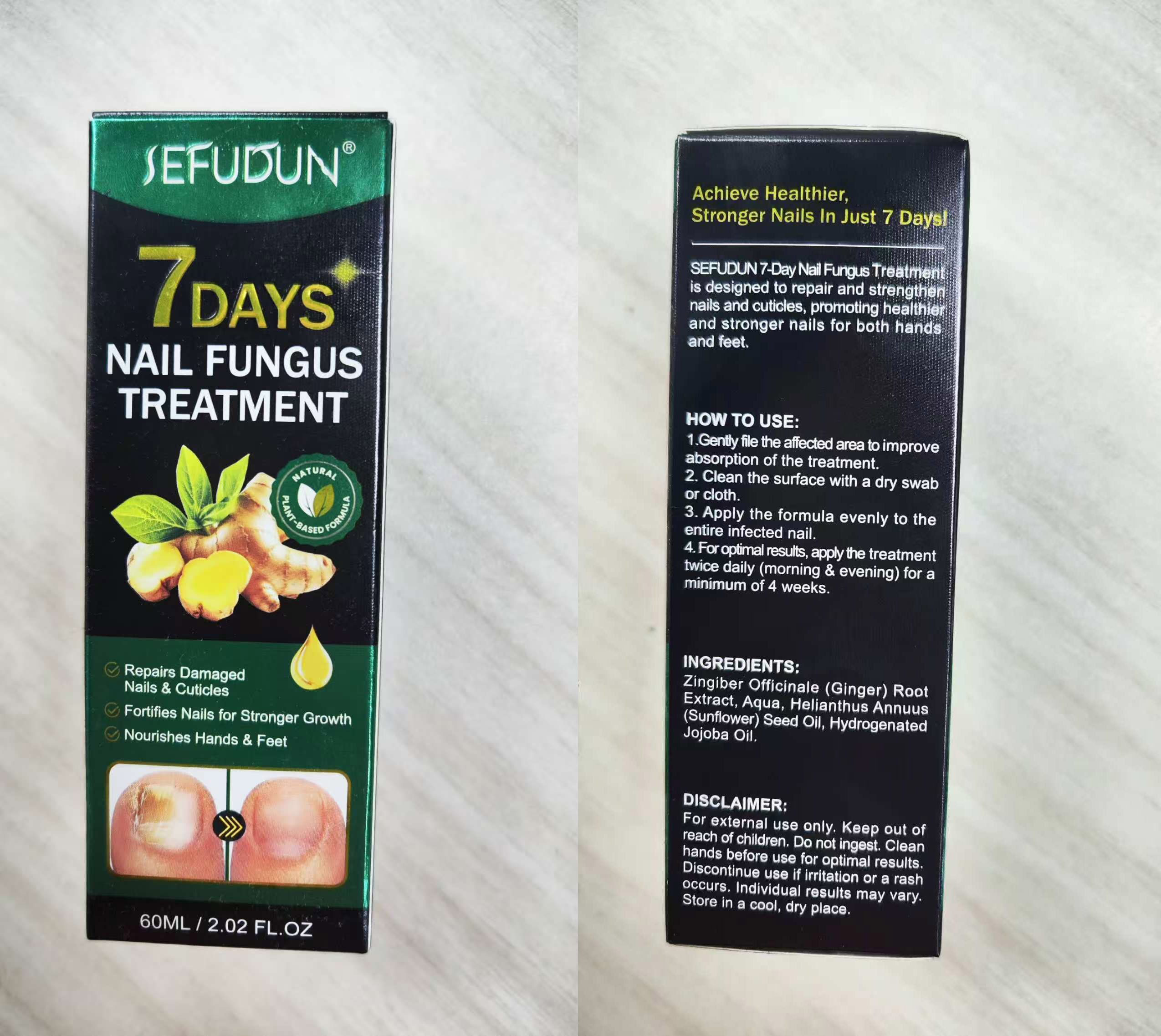 DRUG LABEL: SEFUDUN NAIL FUNGUS TREATMENT
NDC: 83804-002 | Form: LIQUID
Manufacturer: Shenzhen Shandian Jingling Technology Co., Ltd.
Category: otc | Type: HUMAN OTC DRUG LABEL
Date: 20250508

ACTIVE INGREDIENTS: GINGER 30 g/60 mL
INACTIVE INGREDIENTS: HYDROGENATED JOJOBA OIL; HELIANTHUS ANNUUS (SUNFLOWER) SEED OIL; AQUA

83804-002 SEFUDUN NAIL FUNGUS TREATMENT

ACTIVE INGREDIENT

Zingiber Officinale (Ginger) Root Extract

PURPOSE

NAIL FUNGUS TREATMENT

KEEP OUT OF REACH OF CHILDREN SECTION

INDICATIONS AND USAGE

SEFUDUN 7-Day Nail Fungus Treatment is designed to repair and strengthen nails and cuticles, promoting healthier and stronger nails for both handsand feet.

WARNINGS

For external use only

DOSAGE AND ADMINISTRATION

HOW TO USE:
1.Gently file the affected area to improveabsorption of the treatment.
2. Clean the surface with a dry swabor cloth.
3. Apply the formula evenly to theentire infected nail.
4. For optimal results, apply the treatmenttwice daily (morning & evening) for aminimum of 4 weeks

INACTIVE INGREDIENT

Aqua
Helianthus Annuus (Sunflower) Seed Oil
Hydrogenated Jojoba Oil